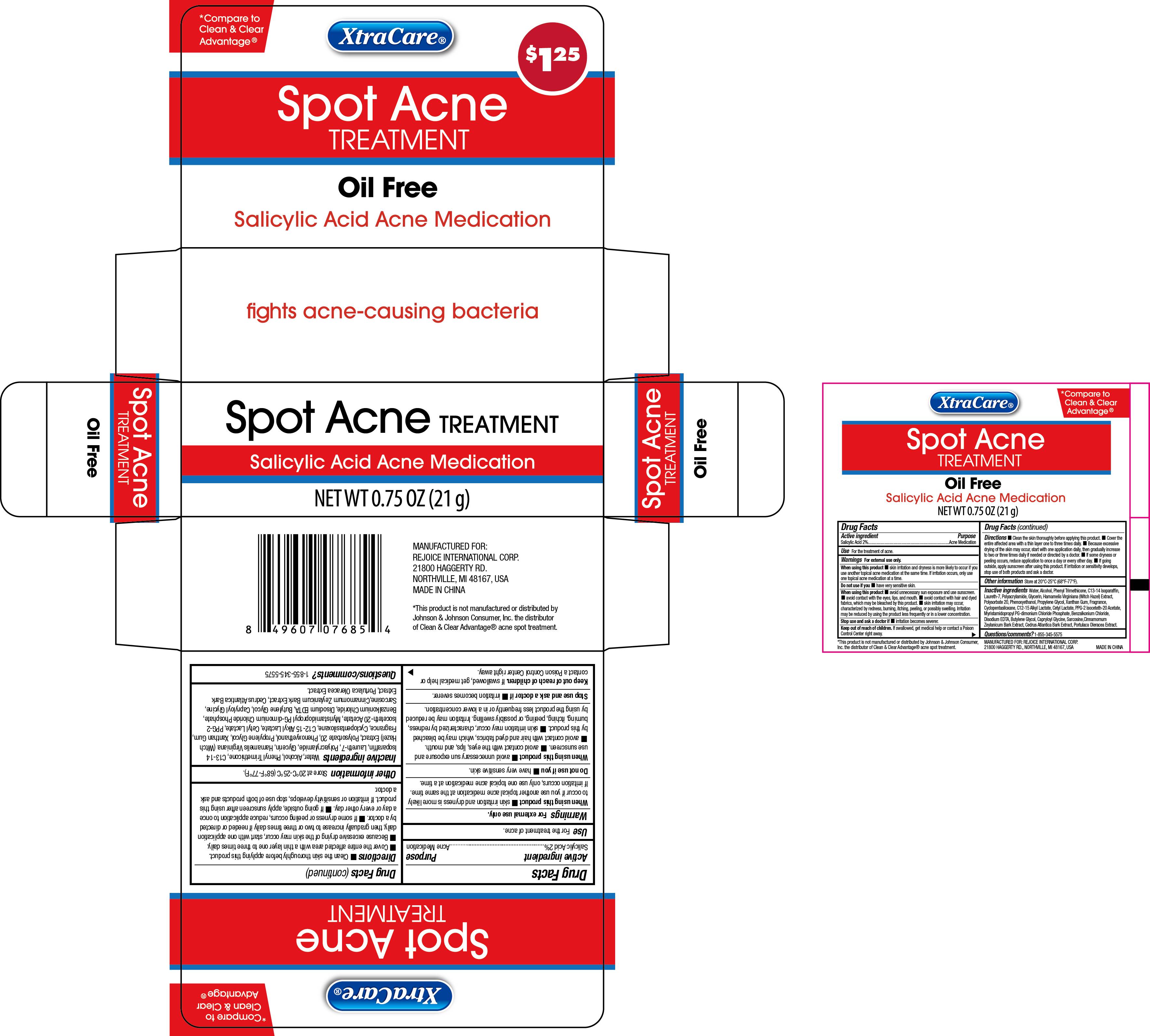 DRUG LABEL: Spot Acne Treatment Oil Free 0.75oz
NDC: 58503-204 | Form: CREAM
Manufacturer: China Ningbo Shangge Cosmetics Technology Corp.
Category: otc | Type: HUMAN OTC DRUG LABEL
Date: 20240910

ACTIVE INGREDIENTS: SALICYLIC ACID 2 g/100 g
INACTIVE INGREDIENTS: XANTHAN GUM; CINNAMON BARK OIL; GLYCERIN; CAPRYLOYL GLYCINE; PPG-2 ISOCETETH-20 ACETATE; CEDRUS ATLANTICA BARK; PROPYLENE GLYCOL; LAURETH-7; PHENOXYETHANOL; CYCLOMETHICONE 5; BUTYLENE GLYCOL; ALCOHOL; PHENYL TRIMETHICONE; POLYSORBATE 20; C12-15 ALKYL LACTATE; SARCOSINE; C13-14 ISOPARAFFIN; HAMAMELIS VIRGINIANA LEAF; EDETATE DISODIUM; WATER; POLYACRYLAMIDE (CROSSLINKED; 2 MOLE PERCENT BISACRYLAMIDE); MYRISTAMIDOPROPYL PG-DIMONIUM CHLORIDE PHOSPHATE; CETYL LACTATE; BENZALKONIUM CHLORIDE; PURSLANE

Active ingredient

Salicylic Acid 2%

Purpose

Acne Medication

Use

For the treatment of acne

Warnings

When using this product
skin irritation and dryness is more likely to occur if you use another topical cene medication at the same time. If irritation occurs, only use one topical
acne medication at a time.

Do not use if you have very sentitive skin.

When using this product

avoid unnessary sun exposure and use sunscreen.
avoid contact with eyes, lips, and mouth.
avoid contact with hair and dyed fabrics, which may be bleached by this product.
skin irritation may occur, characterized by redness, burning, itching, peeling, or possibly swelling. Irritation may be reduced by using the product less
frequently or a lower concentration.

Stop use and ask a doctor if

irritation becomes severer.

Keep out of reach of children

If swallowed, get medical help or contact a Poison Control Center right away.

Directions

Clean the skin thoroughly before applying this product.
Cover the entire affected area with a thin layer one to three times daily.
Because excessive drying of the skin may occur, start with one application daily, then gradually increase to two or three times daily if needed or
directed by a doctor.
If some drynesss or peeling occurs, reduce application to once a day or every other day.
If going outside, apply sunscreen after using this product. If irritation or sensitivity develops, stop use of both products and ask a doctor.

Other information

Store at 20°C-25°C (68°F-77°F)

Inactive gredients

Water
Alcohol
Phenyl Trimethicone
C13-14 Isoparaffin
Laureth-7
Polyacrylamide
Glycerin
Hamamelis Virginiana (Witch Hazel) Exact
Polysorbate 20
Phenoxyethanol
Propylene Glycol
Xanthan Gum
Fragrance
Cyclopentasiloxane

C12-15 Alkyl Lactate
Cetyl Lactate,
PPG-2 Isoceteth-20 Acetate
Myristamidopropyl PG-dimonium Chloride Phosphate
Benzalkonium Chloride,
Disodium EDTA,
Butylene Glycol,
Capryloyl Glycine,
Sarcosine
Cinnamomum Zeylanicum Bark Extract,
Cedrus Atantica Bark Extract,
Portulaca Oleracea Extact